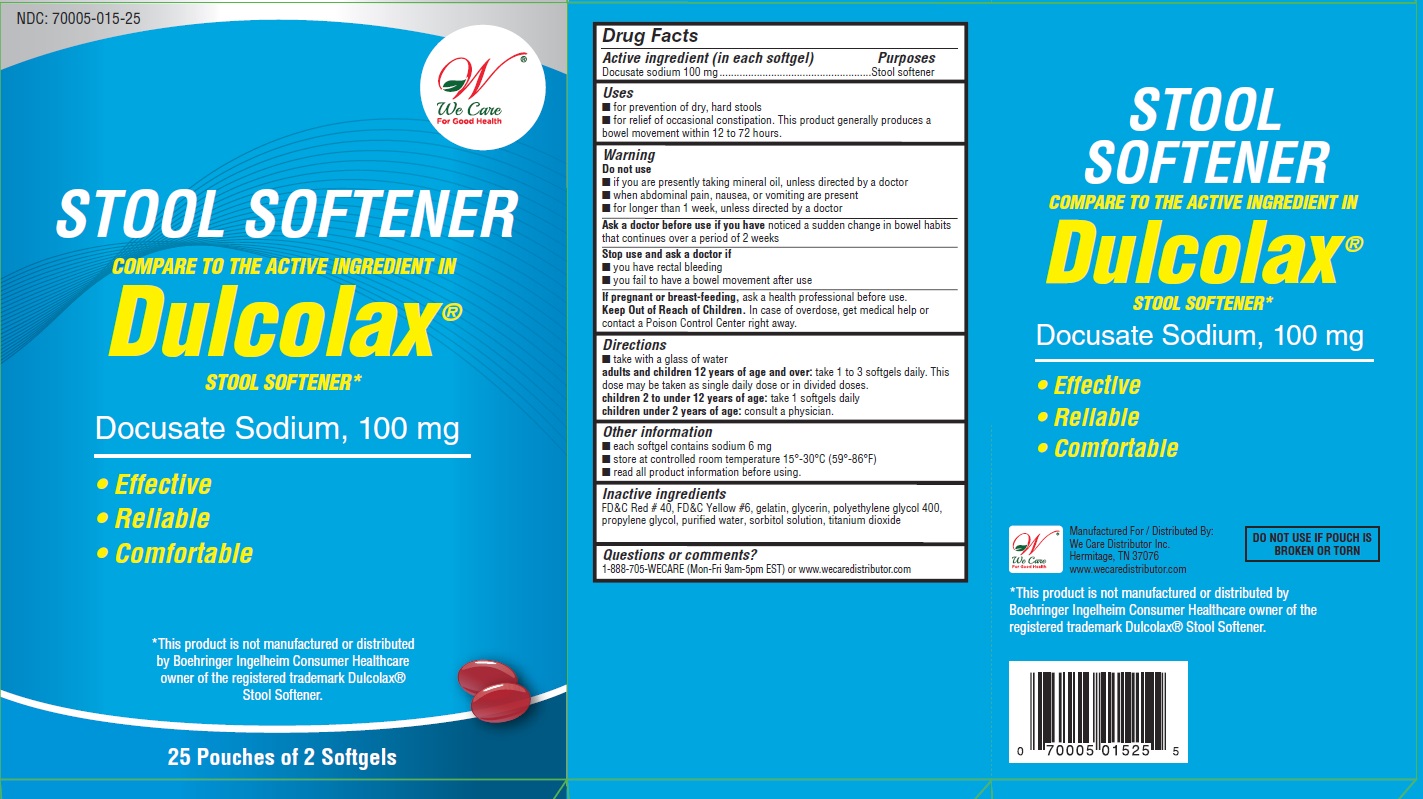 DRUG LABEL: STOOL SOFTENER
NDC: 70005-015 | Form: CAPSULE, LIQUID FILLED
Manufacturer: We Care Distributor Inc.
Category: otc | Type: HUMAN OTC DRUG LABEL
Date: 20160309

ACTIVE INGREDIENTS: DOCUSATE SODIUM 200 mg/1 1
INACTIVE INGREDIENTS: FD&C RED NO. 40; FD&C YELLOW NO. 6; GELATIN; GLYCERIN; POLYETHYLENE GLYCOL 400; PROPYLENE GLYCOL; SORBITOL; TITANIUM DIOXIDE; WATER

STOOL SOFTENER - Docusate Sodium Softgels, 100 mg

Drug Facts

ACTIVE INGREDIENT

Active ingredient (in each softgel) Purpose

Docusate sodium 100 mg..............................Stool softener

Uses

■ for prevention of dry, hard stools

■ for relief of occasional constipation. This product generally produces a bowel movement within 12 to 72 hours.

Warnings

Do not use

■ if you are presently taking mineral oil, unless directed by a doctor

■ when abdominal pain, nausea, or vomiting are present

■ for longer than 1 week, unless directed by a doctor

Ask a doctor before use if you have

noticed a sudden change in bowel habits that continues over a period of 2 weeks

Stop use and ask a doctor if

■ you have rectal bleeding

■ you fail to have a bowel movement after use

PREGNANCY OR BREAST FEEDING

If pregnant or breast-feeding, ask a health professional before use.

Keep out of reach of children.

In case of overdose, get medical help or contact a Poison Control Center right away.

Directions

■ take with a glass of water

■ adults and children 12 years of age and over: take 1 to 3 softgels daily. This dose may be taken as single daily dose or in divided doses.

■ children 2 to under 12 years of age: take 1 softgels daily

■ children under 2 years of age: consult a physician.

Other information

■ each softgel contains sodium 6 mg

■ store at controlled room temperature 15°-30°C (59°-86°F)

■ read all product information before using

Inactive ingredients

FD&C Red # 40, FD&C Yellow #6, gelatin, glycerine, polyethylene glycol 400, propylene glycol, purified water, sorbitol solution, titanium dioxide

Questions or comments?

1-888-705-WECARE (Mon-Fri 9am-5pm EST) or www.wecaredistributor.com

PRINCIPAL DISPLAY PANEL

Compare to the Active Ingredients in Dulcolax® Stool Softener

STOOL SOFTENER

Docusate Sodium Softgels, 100 mg

TO OPEN
PUSH IN TAB AND PULL OUT

25 Pouches of 2 Softgels Each